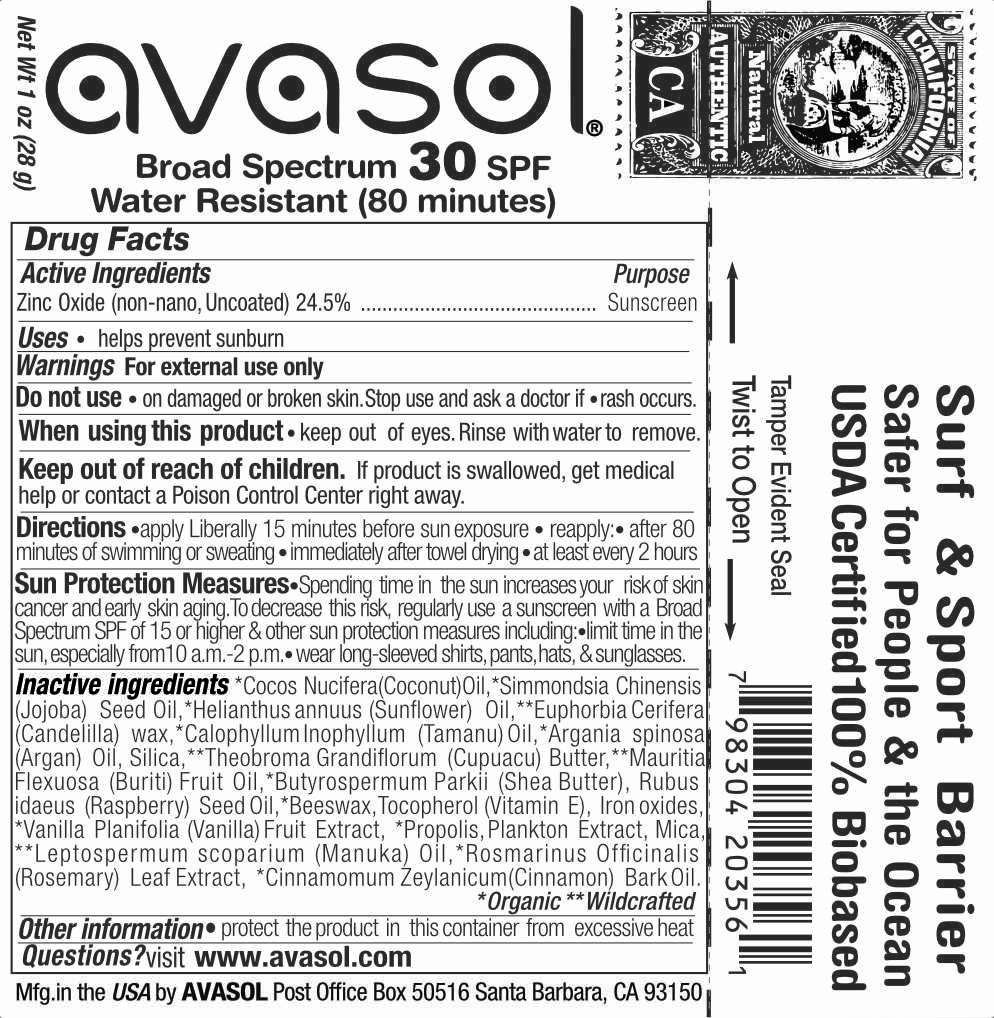 DRUG LABEL: Surfers Barrier
NDC: 58518-020 | Form: STICK
Manufacturer: Avasol LLC
Category: otc | Type: HUMAN OTC DRUG LABEL
Date: 20260126

ACTIVE INGREDIENTS: ZINC OXIDE 24.5 g/100 g
INACTIVE INGREDIENTS: COCONUT OIL; JOJOBA OIL; SUNFLOWER OIL; CANDELILLA WAX; TAMANU OIL; ARGAN OIL; SILICON DIOXIDE; THEOBROMA GRANDIFLORUM SEED; SHEANUT; MAURITIA FLEXUOSA WHOLE; RUBUS IDAEUS SEED; YELLOW WAX; TOCOPHEROL; FERROUS OXIDE; VANILLA BEAN; PROPOLIS WAX; MICA; HAEMATOCOCCUS PLUVIALIS; MANUKA OIL; ROSEMARY; CINNAMON BARK OIL

Surfers Barrier Stick SPF 30

Drug Facts

Active Ingredients

Zinc Oxide (non-nano, Uncoated) 24.5%

Purpose

Sunscreen

Uses

- helps prevent sunburn

Warnings

- For external use only.
- Keep out of eyes. Rinse with water to remove.

Stop use and ask a doctor if rash or irritation occurs.

Do not use if allergic to ingredients, or nuts. Test small area first.

Keep out of reach of children. lf swallowed, get medical help right away.

Directions

- apply liberally before sun
- reapply: after 80 min. of swimming or sweating, immediately after towel drying, or as needed
- children under 6 months: Ask a doctor.

Inactive ingredients

*Cocos Nucifera (Coconut) Oil,*Simmondsia Chinensis (Jojoba) Seed Oil, *Helianthus annuus (Sunflower) Oil, **Euphorbia Cerifera (Candelilla) wax, *Calophyllum Inophyllum (Tamanu) Oil, *Argania spinosa (Argan) Oil, Silica, **Theobroma Grandiflorum (Cupuacu) Butter, **Mauritia Flexuosa (Buriti) Fruit Oil, *Butyrospermum Parkii (Shea Butter), Rubus idaeus (Raspberry) Seed Oil, *Beeswax, Tocopherol (Vitamin E), Iron oxides, *Vanilla Planifolia (Vanilla) Fruit Extract, *Propolis, Plankton Extract, Mica, **Leptospermum scoparium (Manuka) Oil, *Rosmarinus Officinalis (Rosemary) Leaf Extract, *Cinnamomum Zeylanicum (Cinnamon) Bark Oil. **Organic **Wildcrafted

Other information

- protect package from moisture & extreme heat

Questions?

visit www.avasol.com

Principal Display Panel - 1oz Tube Label

avasol®

mineral sunscreen

30 SPF

Surf & Sport Barrier Water-resistant (80 min.)

Broad Spectrum (UVA/UVB) People-safe

- Ocean-safe Authentic
- 100% Bio-based

Net Wt 1oz (28 g)